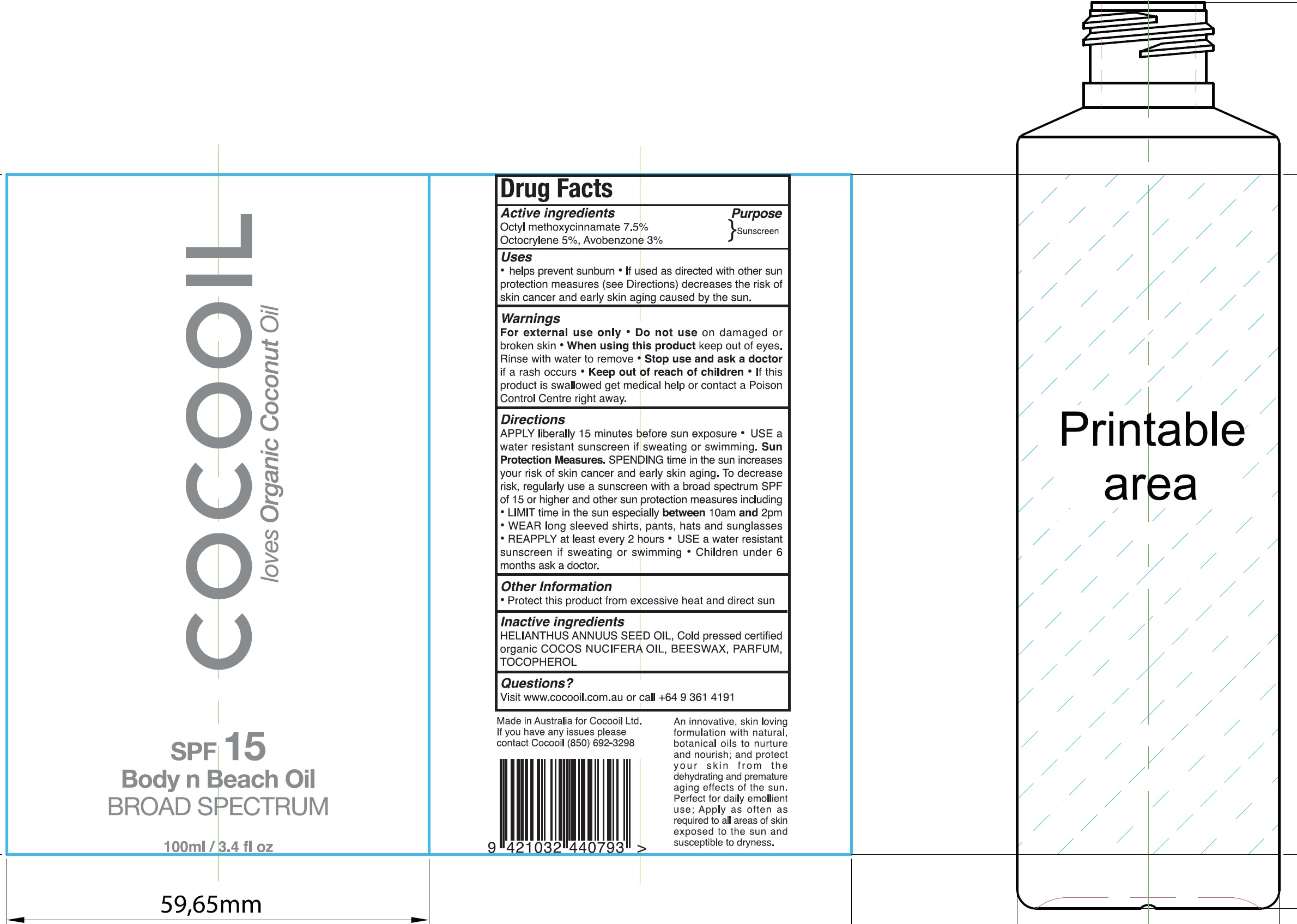 DRUG LABEL: Cocooil SPF15
NDC: 72645-001 | Form: LOTION
Manufacturer: Cocooil Limited
Category: otc | Type: HUMAN OTC DRUG LABEL
Date: 20200504

ACTIVE INGREDIENTS: OCTINOXATE 75 mg/1 mL; OCTOCRYLENE 50 mg/1 mL; AVOBENZONE 30 mg/1 mL
INACTIVE INGREDIENTS: SUNFLOWER OIL; YELLOW WAX; TOCOPHEROL

Cocooil SPF15

Active ingredients

Octyl methoxycinnamate 7.5%

Octocrylene 5%, Avobenzone 3%

Purpose

Sunscreen

Uses

- helps prevent sunburn
- If used as directed with other sun protection measures (see Directions) decreases the risk of skin cancer and early skin aging caused by the sun.

Warnings

For external use ony

Do not use

- on damaged or broken skin

When using this product

- keep out of eyes. Rinse with water to remove

Stop use and ask a doctor

- if a rash occurs

Keep out of reach of children

- If this product is swallowed get medical help or contact a Poison Control Center right away.

Directions

APPLY liberally 15 minutes before sun exposure

- USE a water resistant sunscreen if sweating or swimming. Sun Protection Measures. SPENDING time in the sun increases your risk of skin cancer and early skin aging. To decreases risk, regularly use a sunsreen with a broad spectrum SPF of 15 or higher and other sun protection measures including
- LIMIT time in the sun especially between 10am and 2pm
- WEAR long sleeved shirts, pants, hats and sunglasses
- REAPPLY at least every 2 hours
- USE a water resistant sunscreen if sweating or swimming
- Children under 6 months ask a doctor.

Other Information

- Protect this product from excessive heat and direct sun

Inactive ingrediets

HELIANTHUS ANNUUS SEED OIL, Cold pressed certified organic COCOS NUCIFERA OIL, BEESWAX, PARFUM, TOCOPHEROL

Questions?

Visit www.cocooil.com.au or call +64 9 361 4191